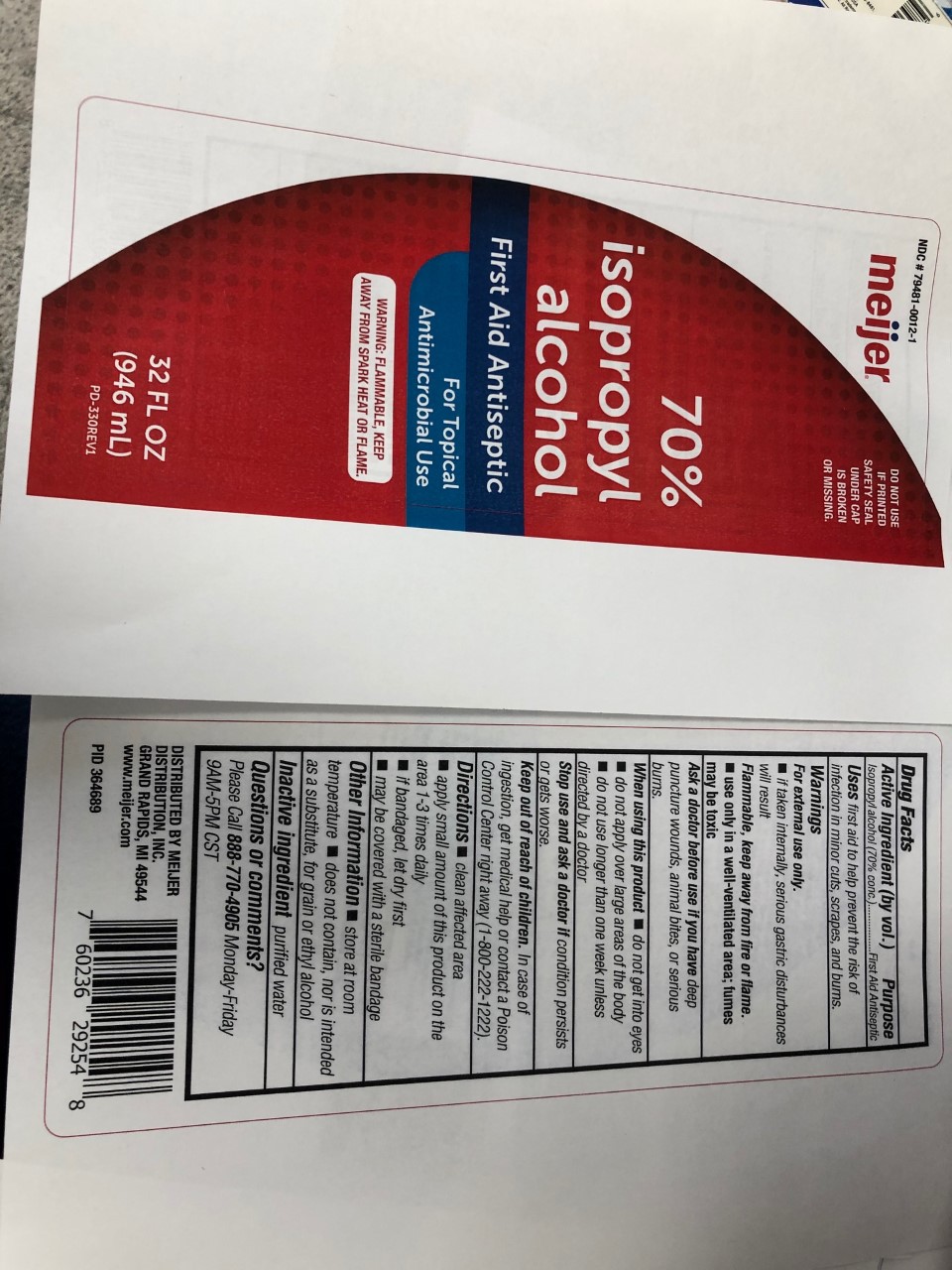 DRUG LABEL: 70% Isopropyl Alcohol
NDC: 79481-0012 | Form: LIQUID
Manufacturer: Meijer
Category: otc | Type: HUMAN OTC DRUG LABEL
Date: 20210310

ACTIVE INGREDIENTS: ISOPROPYL ALCOHOL 70 mL/100 mL
INACTIVE INGREDIENTS: WATER

Meijer 70% IPA

This is a first aid antiseptic. It is manufactured using only the following United States Pharmacopoeia (USP) grade ingredients:

1. Isopropyl Alcohol (70%, v/v) in an aqueous solution
2. Sterile distilled water or boiled cold water.

The firm does not add other active or inactive ingredients.

Active Ingredient(s)

Isopropyl Alcohol 70% v/v. Purpose: Antiseptic

Purpose

Antiseptic.

Use

First aid to help prevent the risk of infection in minor cuts, scrapes, and burns.

Warnings

For external use only. If taken internally, serious gastric disturbances will result. Flammable. Keep away from heat or flame. Use only in a well-ventilated area; fumes may be toxic.

Do not use

- do not apply over large areas of the body
- do not use longer than one week unless directed by a doctor

When using this product do not get in eyes

do not apply over large areas of the body

do not use longer than one week unless directed by a doctor

Stop use and ask a doctor if irritation or rash occurs. These may be signs of a serious condition.

Keep out of reach of children. If swallowed, get medical help or contact a Poison Control Center right away.

Directions

- Clean affected area
- apply small amount of this product on the area 1-3 times daily
- if bandaged, let dry first
- may be covered with a sterile bandage

Other information

- Store at room temperature
- does not contain, nor is intended as a substitute, for grain or ethyl alcohol

Inactive ingredients

purified water

Package Label - Principal Display Panel

946 ml NDC: 79481-0012-1